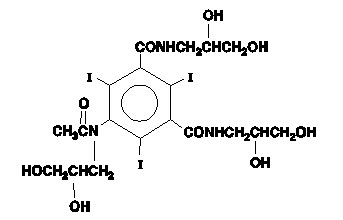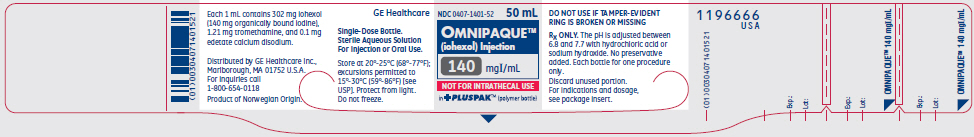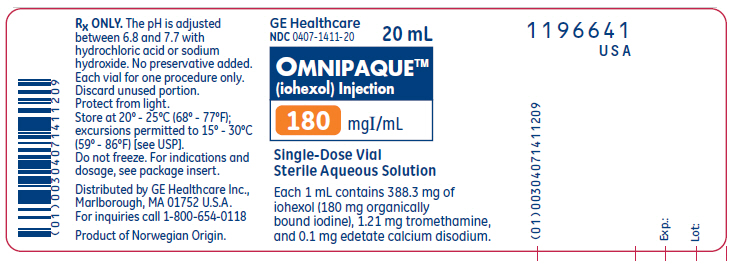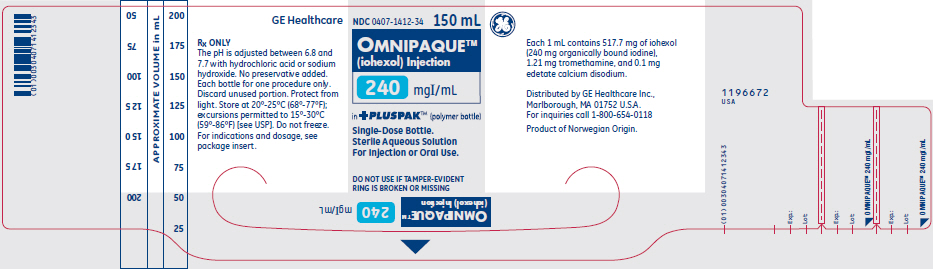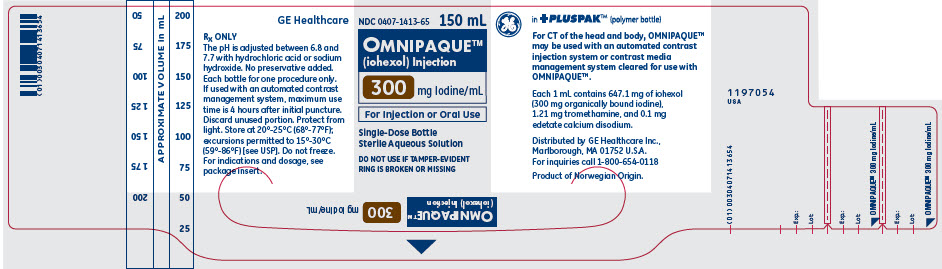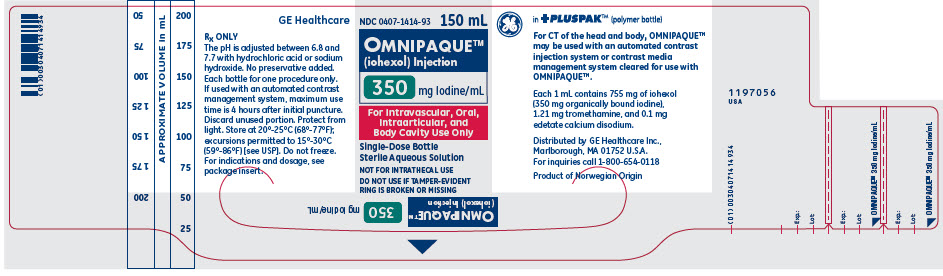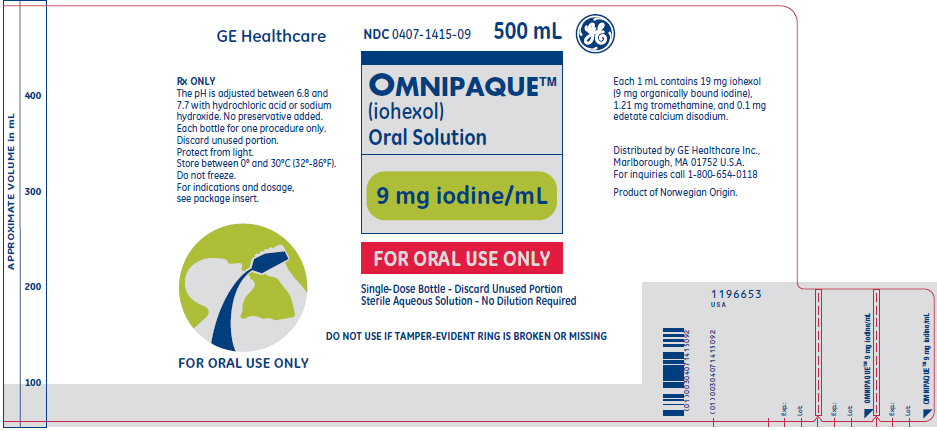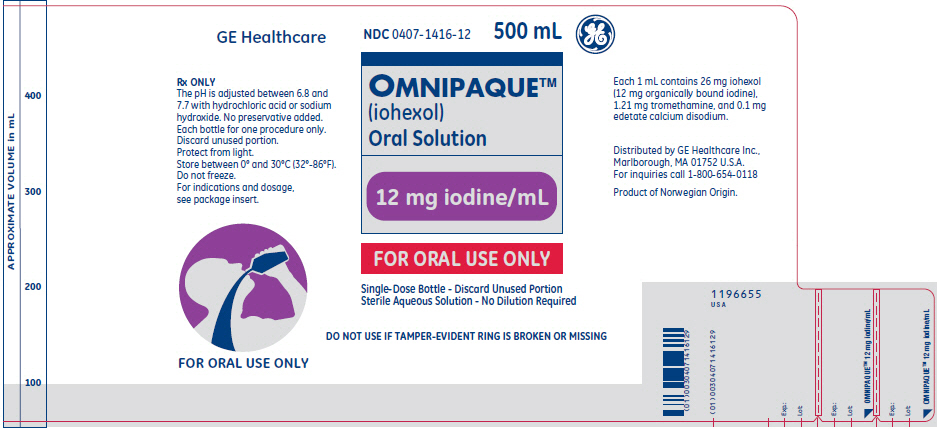 DRUG LABEL: OMNIPAQUE
NDC: 0407-1401 | Form: INJECTION, SOLUTION
Manufacturer: GE Healthcare Inc.
Category: prescription | Type: HUMAN PRESCRIPTION DRUG LABEL
Date: 20241017

ACTIVE INGREDIENTS: Iohexol 140 mg/1 mL
INACTIVE INGREDIENTS: tromethamine 1.21 mg/1 mL; edetate calcium disodium 0.1 mg/1 mL; hydrochloric acid; sodium hydroxide

HIGHLIGHTS OF PRESCRIBING INFORMATION

These highlights do not include all the information needed to use OMNIPAQUE safely and effectively. See full prescribing information for OMNIPAQUE.
OMNIPAQUE (iohexol) injection, for intrathecal, intra-arterial, intravenous, oral, rectal, intraarticular, or body cavity use
OMNIPAQUE (iohexol) oral solution
Initial U.S. Approval: 1985

WARNING: RISKS ASSOCIATED WITH INTRATHECAL ADMINISTRATION OF OMNIPAQUE INJECTION 140 mg IODINE/mL and 350 mg IODINE/mL

WARNING: RISKS ASSOCIATED WITH INTRATHECAL ADMINISTRATION OF OMNIPAQUE INJECTION 140 and 350 mg IODINE/mL

Use only the iodine concentrations and presentations recommended for intrathecal procedures. Intrathecal administration of a wrong iodine concentration, even if inadvertent, may cause death, convulsions, seizures, cerebral hemorrhage, coma, paralysis, arachnoiditis, acute renal failure, cardiac arrest, rhabdomyolysis, hyperthermia, and brain edema. (2.2, 2.8, 5.1)

RECENT MAJOR CHANGES

Indications and Usage, CT cerebral ventriculography (1.1) - Removed | 10/2024
Dosage and Administration (2.6, 2.10, 2.11) | 10/2024

1 INDICATIONS AND USAGE

OMNIPAQUE is a radiographic contrast agent indicated for intrathecal, intra-arterial, intravenous, oral, rectal, intraarticular, and body cavity imaging procedures in adults and pediatric patients. (1)

2 DOSAGE AND ADMINISTRATION

- For each imaging procedure, specific dosage forms, concentrations, and presentations are recommended.
- Individualize the concentration and volume according to the specific dosing tables and accounting for factors such as age, body weight, and condition of the patient, and the equipment and imaging technique used. (2.2, 2.3, 2.4, 2.5, 2.6, 2.7, 2.8, 2.9)
- See full prescribing information for complete dosing and administration information. (2)

3 DOSAGE FORMS AND STRENGTHS

- Injection: 140 mg iodine/mL, 180 mg iodine/mL, and 240 mg iodine/mL in single-dose vials/bottles; 300 mg iodine/mL and 350 mg iodine/mL in single-dose vials/bottles and imaging or pharmacy bulk package
- Oral Solution: 9 mg iodine/mL and 12 mg iodine/mL (3)

4 CONTRAINDICATIONS

- Hysterosalpingography during pregnancy (or suspected pregnancy), menstruation (or when menstruation is imminent), within 6 months after termination of pregnancy, within 30 days after conization or curettage, when signs of infection are present in any portion of the genital tract, including the external genitalia, and when reproductive tract neoplasia is known or suspected. (4)

5 WARNINGS AND PRECAUTIONS

- Hypersensitivity Reactions: Life-threatening or fatal reactions can occur. Always have emergency equipment and trained personnel available. (5.3)
- Acute Kidney Injury: Acute injury including renal failure can occur. Minimize dose and maintain adequate hydration to minimize risk. (5.4)
- Cardiovascular Adverse Reactions: Hemodynamic disturbances including shock and cardiac arrest may occur during or after administration. (5.5)
- Thyroid Dysfunction in Pediatric Patients 0 to 3 Years of Age: Individualize thyroid function monitoring based on risk factors such as prematurity. (5.9)

6 ADVERSE REACTIONS

Most common adverse reactions (incidence ≥ 1%) in adult patients

- Intrathecal: Headaches, pain including backache, neckache, stiffness and neuralgia, nausea, vomiting, dizziness
- Intra-arterial or intravenous: Pain, vision abnormalities (including blurred vision and photomas), headache, taste perversion, arrhythmias including premature ventricular contractions (PVCs) and premature atrial contractions (PACs), angina/chest pain, nausea
- Oral: Diarrhea, nausea, vomiting, abdominal pain, flatulence, headache
- Body Cavity: Pain, swelling, heat sensation (6.1)

To report SUSPECTED ADVERSE REACTIONS, contact GE Healthcare at 1-800-654-0118 or FDA at 1-800-FDA-1088 or www.fda.gov/medwatch.

8 USE IN SPECIFIC POPULATIONS

- Lactation: A lactating woman may pump and discard breast milk for 10 hours after OMNIPAQUE administration. (8.2)

FULL PRESCRIBING INFORMATION

WARNING: RISKS ASSOCIATED WITH INTRATHECAL ADMINISTRATION OF OMNIPAQUE INJECTION 140 mg IODINE/mL and 350 mg IODINE/mL

Use only the OMNIPAQUE iodine concentrations and presentations recommended for intrathecal procedure [see Dosage and Administration (2.2, 2.8)]. Intrathecal administration of OMNIPAQUE of a wrong iodine concentration, even if inadvertent, may cause death, convulsions, seizures, cerebral hemorrhage, coma, paralysis, arachnoiditis, acute renal failure, cardiac arrest, rhabdomyolysis, hyperthermia, and brain edema [see Warnings and Precautions (5.1)].

1 INDICATIONS AND USAGE

1.1 Intrathecal Procedures‡

OMNIPAQUE is indicated for:

- Myelography and computerized tomography (CT) myelography (lumbar, thoracic, cervical, total columnar) in adults and pediatric patients aged 2 weeks and older
- CT cisternography in adults and pediatric patients aged 2 weeks and older

1.2 Intra-arterial Procedures‡

OMNIPAQUE is indicated for:

- Cardiac ventriculography in adults and pediatric patients
- Aortography including studies of aorta and its branches in adults and pediatric patients
- Selective coronary arteriography in adults
- Cerebral arteriography in adults
- Peripheral arteriography in adults
- Intra-arterial digital subtraction angiography (IA-DSA) of the head, neck, abdominal, renal, and peripheral vessels in adults
- Pulmonary angiography in pediatric patients

1.3 Intravenous Procedures‡

OMNIPAQUE is indicated for:

- Excretory urography in adults and pediatric patients
- CT of the head and body in adults and pediatric patients
- Peripheral venography (phlebography) in adults
- Intravenous digital subtraction angiography (IV-DSA) of the head, neck, abdominal, renal, and peripheral vessels in adults

1.4 Oral or Rectal Procedures‡

OMNIPAQUE is indicated for:

- Radiographic examination of the gastrointestinal (GI) tract in adults and pediatric patients
- CT of the abdomen and pelvis in conjunction with intravenous administration of OMNIPAQUE in adults and pediatric patients

1.5 Intraarticular Procedures‡

OMNIPAQUE is indicated for:

- Arthrography in adults

1.6 Body Cavity Procedures‡

OMNIPAQUE is indicated for:

- Endoscopic retrograde pancreatography (ERP) and cholangiopancreatography (ERCP) in adults
- Herniography in adults
- Hysterosalpingography in adults
- Voiding cystourethrography (VCU) in pediatric patients

‡ Specific dosage forms, concentrations, and presentations of OMNIPAQUE are recommended for each type of imaging procedure [see Dosage and Administrations (2.2, 2.3, 2.4, 2.5, 2.6, 2.7, 2.8, 2.9) and Warnings and Precautions (5.1, 5.2)].

2 DOSAGE AND ADMINISTRATION

2.1 Important Dosage and Administration Instructions

- Specific dosage forms, concentrations, and presentations of OMNIPAQUE are recommended for each type of imaging procedure [see Dosage and Administration (2.2, 2.3, 2.4, 2.5, 2.6, 2.7, 2.8, 2.9) and Warnings and Precautions (5.1, 5.2)].
- Individualize the volume, strength, and rate of administration of OMNIPAQUE injection according to the specific dosing tables [see Dosage and Administration (2.2, 2.3, 2.4, 2.5, 2.6, 2.7, 2.8, 2.9)]. Consider factors such as age, body weight, vessel size, blood flow rate within the vessel, anticipated pathology, degree and extent of opacification required, structures or area to be examined, disease processes affecting the patient, and equipment and technique to be employed.
- Hydrate patients before and after administration of OMNIPAQUE injection [see Warnings and Precautions (5.4)].
- Use aseptic technique for all handling and administration of OMNIPAQUE injection.
- Administer OMNIPAQUE injection at either body (37°C, 98.6°F) or room temperature (20°C to 25°C, 68°F to 77°F).
- Do not mix OMNIPAQUE injection with, or inject in intravenous lines containing, other drugs or total nutritional admixtures except when OMNIPAQUE injection is administered in an automated contrast injection system or contrast management system suitable for simultaneous injection of OMNIPAQUE injection and 0.9% Sodium Chloride Injection [see Dosage and Administration (2.10, 2.11)].
- Parenteral drug products should be inspected visually for particulate matter and discoloration prior to administration, whenever solution and container permit.
- Each container of OMNIPAQUE injection and OMNIPAQUE oral solution in single-dose containers are intended for one procedure only. Discard any unused portion.

2.2 Recommended Dosage for Intrathecal Procedures in Adults

- The recommended doses for intrathecal procedures in adults are shown in Table 1.
- Administer over 1 minute to 2 minutes.
- If sequential or repeat examinations are required, allow at least 48 hours for clearance of the drug from the body before repeat administration; however, whenever possible, 5 days to 7 days is recommended.
- If CT myelography is performed, delay imaging by several hours to reduce the degree of contrast.

Table 1. Recommended Concentrations and Volumes of OMNIPAQUE Injection for Intrathecal Procedures in Adults
Imaging Procedure | Injection Type | Concentration (mg Iodine/mL) | Volume to Administer
Lumbar Myelography | Lumbar | 180 [Use single-dose containers or 500 mL Pharmacy Bulk Packages [see Dosage and Administration (2.11)].] | 10 mL to 17 mL
Lumbar Myelography | Lumbar | 240 | 7 mL to 12.5 mL
Thoracic Myelography | Lumbar Cervical | 240 | 6 mL to 12.5 mL
Thoracic Myelography | Lumbar Cervical | 300 | 6 mL to 10 mL
Cervical Myelography | Lumbar | 240 | 6 mL to 12.5 mL
Cervical Myelography | Lumbar | 300 | 6 mL to 10 mL
Cervical Myelography | C1-2 | 180 | 7 mL to 10 mL
Cervical Myelography | C1-2 | 240 | 6 mL to 12.5 mL
Cervical Myelography | C1-2 | 300 | 4 mL to 10 mL
Total Columnar Myelography | Lumbar | 240 | 6 mL to 12.5 mL
Total Columnar Myelography | Lumbar | 300 | 6 mL to 10 mL
CT Cisternography | Lumbar | 180 | 10 mL to 17 mL
CT Cisternography | Lumbar | 240 | 7 mL to 12.5 mL

2.3 Recommended Dosage for Intra-arterial Procedures in Adults

The recommended doses for intra-arterial procedures in adults are shown in Table 2.

Table 2. Recommended Concentrations and Volumes of OMNIPAQUE Injection for Intra-arterial Procedures in Adults
Imaging Procedure |  | Concentration (mg Iodine/mL) | Volume to Administer per Single Injection for Selective Injection Sites | Maximum Cumulative Total Dose
Cardiac Ventriculography |  | 350 [Use single-dose containers or a 500 mL Pharmacy Bulk Package [see Dosage and Administration (2.11)].] | 40 mL (Range of 30 mL to 60 mL) may be combined with selective coronary arteriography | 250 mL
Aortography and Selective Visceral Arteriography |  | 300 | - Aorta (aortic arch, ascending aorta): 50 mL to 80 mL - Abdominal aorta and its branches (celiac, mesenteric, hepatic, and splenic arteries): 30 mL to 60 mL - Renal arteries: 5 mL to 15 mL | 290 mL
Aortography and Selective Visceral Arteriography |  | 350 | - Aorta (aortic arch, ascending aorta): 50 mL to 80 mL - Abdominal aorta and its branches (celiac, mesenteric, hepatic, and splenic arteries): 30 mL to 60 mL - Renal arteries: 5 mL to 15 mL | 250 mL
Aortic root and arch study when used alone |  | 350 | 50 mL (Range of 20 mL to 75 mL) | 250 mL
Selective Coronary Arteriography |  | 350 | 5 mL (Range of 3 mL to 14 mL) | 250 mL
Cerebral Arteriography |  | 300 | - Common carotid artery: 6 mL to 12 mL - Internal carotid artery: 8 mL to 10 mL - External carotid artery: 6 mL to 9 mL - Vertebral artery: 6 mL to 10 mL | 290 mL
Peripheral Arteriography | Aortofemoral Runoffs | 300 | 30 mL to 90 mL | 290 mL
Peripheral Arteriography | Aortofemoral Runoffs | 350 | 20 mL to 70 mL | 250 mL
Peripheral Arteriography | Selective Arteriogram | 300 | 10 mL to 60 mL | 290 mL
Peripheral Arteriography | Selective Arteriogram | 350 | 10 mL to 30 mL | 250 mL
IA-DSA (head, neck, abdominal, renal, and peripheral vessels) |  | 140 | - Aorta: 20 mL to 45 mL at 8 mL/sec to 20 mL/sec - Carotid artery: 5 mL to 10 mL at 3 mL/sec to 6 mL/sec - Femoral artery: 9 mL to 20 mL at 3 mL/sec to 6 mL/sec - Vertebral artery: 4 mL to 10 mL at 2 mL/sec to 8 mL/sec - Renal arteries: 6 mL to 12 mL at 3 mL/sec to 6 mL/sec - Other branches of aorta (includes subclavian, axillary, innominate, and iliac): 8 mL to 25 mL at 3 mL/sec to 10 mL/sec | 250 mL

2.4 Recommended Dosage for Intravenous Procedures in Adults

The recommended doses for intravenous procedures in adults are shown in Table 3.

Table 3. Recommended Concentrations and Volumes of OMNIPAQUE Injection for Intravenous Procedures in Adults
Imaging Procedure |  | Concentration (mg Iodine/mL) | Volume to Administer
Excretory Urography |  | 300 [Use single-dose containers or 500 mL Pharmacy Bulk Packages [see Dosage and Administration (2.11)].] | 0.6 mL/kg to 1.2 mL/kg body weight (maximum dose is 102 mL)
Excretory Urography |  | 350 | 0.6 mL/kg to 1.2 mL/kg body weight (maximum dose is 102 mL)
CT | Head | 240 | 120 mL to 250 mL by infusion
CT | Head | 300 [Use single-dose containers, 500 mL Imaging Bulk Packages or Pharmacy Bulk Packages, or 150 mL single-dose bottles with an automated contrast injection system or contrast management system [see Dosage and Administration (2.10, 2.11, 2.12)].] | 70 mL to 150 mL by rapid injection
CT | Head | 350 | 80 mL by rapid injection
CT | Body | 300 | 50 mL to 200 mL by rapid injection
CT | Body | 350 | 60 mL to 100 mL by rapid injection
Peripheral Venography (phlebography) |  | 240 | 20 mL to 150 mL per leg
Peripheral Venography (phlebography) |  | 300 | 40 mL to 100 mL per leg
IV-DSA (head, neck, abdominal, renal, and peripheral vessels) |  | 350 | 30 mL to 50 mL at 7.5 mL/sec to 30 mL/sec using a pressure injector Frequently three or more doses may be required; the maximum cumulative total dose is 250 mL

2.5 Recommended Dosage for Oral Procedures in Adults

Recommended Dosage for Radiographic Examination of the GI Tract in Adults

The recommended dose for radiographic examination of the GI tract in adults is 50 mL to 100 mL of OMNIPAQUE injection 350 mg iodine/mL administered undiluted orally.

Recommended Dosage for CT of the Abdomen and Pelvis in Conjunction with Intravenous Administration of OMINIPAQUE Injection in Adults

The recommended oral dose using diluted OMNIPAQUE injection or OMNIPAQUE oral solution and concurrent intravenous doses for CT of the abdomen and pelvis in adults are shown in Table 4.

Table 4. Recommended Concentrations and Volumes of Diluted OMNIPAQUE Injection or OMNIPAQUE Oral Solution for Oral Administration and Concurrent Intravenous OMNIPAQUE Injection for CT of the Abdomen and Pelvis in Adults
Concentration (mg Iodine/mL) | Volume to Administer | Administration Instructions
Oral Dose Using Diluted OMNIPAQUE Injection
6 mg Iodine/mL to 12 mg Iodine/mL of Diluted OMNIPAQUE Injection [See Table 5 for dilution instructions of OMNIPAQUE injection] | 500 mL to 1,000 mL | - Administer the oral dose all at once or over a period of up to 45 minutes if there is difficulty in consuming the required volume. - Use a higher iodine concentration of the diluted product if a smaller volume needs to be administered (see Table 5).
Oral Dose Using OMNIPAQUE Oral Solution
9 mg Iodine/mL or 12 mg Iodine/mL of OMNIPAQUE Oral Solution | 500 mL to 1,000 mL | Administer the oral dose all at once or over a period of up to 45 minutes if there is difficulty in consuming the required volume.
Intravenous Dose of OMNIPAQUE injection in Conjunction with Oral Administration
300 [Use single-dose containers, 500 mL Imaging or Pharmacy Bulk Packages, or 150 mL single-dose bottles with an automated contrast injection system or contrast management system [see Dosage and Administration (2.10, 2.11, 2.12)].] | 100 mL to 150 mL | Administer up to 40 minutes AFTER consumption of the oral dose.

Preparation of Diluted OMNIPAQUE Injection for Oral Administration for CT of the Abdomen and Pelvis in Adults

- Prepare the diluted OMNIPAQUE injection in water, carbonated beverage, milk, infant formula, or juice just prior to administration according to Table 5.
- Discard any unused portion after the procedure.

Table 5. Volumes of OMNIPAQUE Injection and Added Liquid to Dilute OMNIPAQUE Injection for Oral Administration for CT of the Abdomen in Adults
Concentration of Diluted OMNIPAQUE injection (mg iodine/mL) | Dilution Method 1 |  | Dilution Method 2 |  | Dilution Method 3
Concentration of Diluted OMNIPAQUE injection (mg iodine/mL) | Volume of OMNIPAQUE 240 mg Iodine/mL (mL) | Volume of Added Liquid [Use water, carbonated beverage, milk, infant formula, or juice.] (mL) | Volume of OMNIPAQUE 300 mg Iodine/mL (mL) | Volume of Added Liquid (mL) | Volume of OMNIPAQUE 350 mg Iodine/mL (mL) | Volume of Added Liquid (mL)
6 | 25 | 975 | 20 | 980 | 17 | 983
9 | 38 | 962 | 30 | 970 | 26 | 974
12 | 50 | 950 | 40 | 960 | 35 | 965
15 | 63 | 937 | 50 | 950 | 43 | 957
18 | 75 | 925 | 60 | 940 | 52 | 948
21 | 88 | 912 | 70 | 930 | 60 | 940

2.6 Recommended Dosage for Intraarticular Procedures in Adults

- The recommended doses for intraarticular procedures in adults are shown in Table 6.
- Use passive or active manipulation to disperse the medium throughout the joint space.

Table 6. Recommended Concentrations and Volumes of OMNIPAQUE Injection for Intraarticular Procedures in Adults
Imaging Procedure | Location | Concentration (mg Iodine/mL) | Volume to Administer | Double Contrast/Single Contrast
Arthrography | Knee | 240 [Use single-dose containers or 500 mL Pharmacy Bulk Packages [see Dosage and Administration (2.11)].] | 5 mL to 15 mL | Lower volumes recommended for double-contrast examinations; higher volumes recommended for single-contrast examinations.
Arthrography | Knee | 300 | 5 mL to 15 mL | Lower volumes recommended for double-contrast examinations; higher volumes recommended for single-contrast examinations.
Arthrography | Knee | 350 | 5 mL to 10 mL | Lower volumes recommended for double-contrast examinations; higher volumes recommended for single-contrast examinations.
Arthrography | Shoulder | 300 | 10 mL | Lower volumes recommended for double-contrast examinations; higher volumes recommended for single-contrast examinations.
Arthrography | Temporomandibular | 300 | 0.5 mL to 1 mL | Lower volumes recommended for double-contrast examinations; higher volumes recommended for single-contrast examinations.

2.7 Recommended Dosage for Body Cavity Procedures in Adults

- The recommended doses for body cavity procedures in adults are shown in Table 7.
- Volume to administer may vary depending on individual anatomy and/or disease state.

Table 7. Recommended Concentrations and Volumes of OMNIPAQUE Injection for Body Cavity Procedures in Adults
Imaging Procedure | Concentration (mg Iodine/mL) | Volume to Administer | Route of Administration
Endoscopic retrograde pancreatography (ERP) and cholangiopancreatography (ERCP) | 240 [Use single-dose containers or 500 mL Pharmacy Bulk Packages [see Dosage and Administration (2.11)].] | 10 mL to 50 mL | Intraductal
Herniography | 240 | 15 mL to 20 mL | Intraperitoneal
Herniography | 300 | 15 mL to 20 mL | Intraperitoneal
Hysterosalpingography | 240 | 50 mL | Intrauterine

2.8 Recommended Dosage for Intrathecal, Intra-arterial, and Intravenous Procedures in Pediatric Patients

Recommended Dosage for Intrathecal Procedures in Pediatric Patients Aged 2 Weeks and Older

- Recommended doses based on age for intrathecal procedures in pediatric patients aged 2 weeks and older are shown in Table 8.
- Administer over 1 minute to 2 minutes.
- If sequential or repeat examinations are required, allow at least 48 hours for clearance of the drug from the body before repeat administration; however, whenever possible, 5 days to 7 days is recommended.
- If CT myelography is performed, delay imaging by several hours to reduce the degree of contrast.

Table 8: Recommended Concentrations and Volumes of OMNIPAQUE Injection Based on Age for Intrathecal Procedure in Pediatric Patients Aged 2 Weeks and Older
Imaging Procedure | Injection Type | Age | Concentration (mg Iodine/mL) | Volume to Administer
- Myelography - Lumbar - Thoracic - Cervical - Total Columnar - CT cisternography | Lumbar | 2 weeks up to 3 months | 180 [Use single-dose containers.] | 2 mL to 4 mL
- Myelography - Lumbar - Thoracic - Cervical - Total Columnar - CT cisternography | Lumbar | 3 months up to 36 months | 180 [Use single-dose containers.] | 4 mL to 8 mL
- Myelography - Lumbar - Thoracic - Cervical - Total Columnar - CT cisternography | Lumbar | 3 years up to 7 years | 180 [Use single-dose containers.] | 5 mL to 10 mL
- Myelography - Lumbar - Thoracic - Cervical - Total Columnar - CT cisternography | Lumbar | 7 years up to 13 years | 180 [Use single-dose containers.] | 5 mL to 12 mL
- Myelography - Lumbar - Thoracic - Cervical - Total Columnar - CT cisternography | Lumbar | 13 years to 18 years | 180 [Use single-dose containers.] | 6 mL to 15 mL

Recommended Dosage for Intra-arterial Procedures in Pediatric Patients

The recommended doses for intra-arterial procedures in pediatric patients are shown in Table 9.

Table 9. Recommended Concentrations and Volumes of OMNIPAQUE Injection per Body Weight for Intra-arterial Procedures in Pediatric Patients
Imaging Procedure | Concentration (mg Iodine/mL) | Volume per Body Weight to Administer per Single Injection | Maximum Cumulative Volume
Cardiac Ventriculography | 300 [Use single-dose containers or 500 mL Pharmacy Bulk Packages [see Dosage and Administration (2.11)].] | 1.75 mL/kg (Range of 1.5 mL/kg to 2 mL/kg) | 6 mL/kg up to a total volume of 290 mL
Cardiac Ventriculography | 350 | 1.25 mL/kg (Range of 1 mL/kg to 1.5 mL/kg) | 5 mL/kg up to a total volume of 250 mL
Aortography (aortic root, aortic arch, and descending aorta) | 350 | 1 mL/kg | 5 mL/kg up to a total volume of 250 mL
Pulmonary Angiography | 350 | 1 mL/kg | 5 mL/kg up to a total volume of 250 mL

Recommended Dosage for Intravenous Procedures in Pediatric Patients

The recommended doses for intravenous procedures in pediatric patients are shown in Table 10.

Table 10. Recommended Concentrations and Volumes of OMNIPAQUE Injection per Body Weight for Intravenous Procedures in Pediatric Patients
Imaging Procedure | Concentration (mg Iodine/mL) | Volume per Body Weight to Administer
Excretory Urography | 300 [Use single-dose containers or 500 mL Pharmacy Bulk Packages [see Dosage and Administration (2.11)].] | 0.5 mL/kg to 3 mL/kg (Maximum single dose: 116 mL)
CT of the Head and Body | 240 | 1 mL/kg to 2 mL/kg (with maximum 3 mL/kg) (Maximum single dose: 116 mL)
CT of the Head and Body | 300 [Use single-dose containers, 500 mL Imaging or Pharmacy Bulk Packages, or 150 mL single-dose bottles with an automated contrast injection system or contrast management system [see Dosage and Administration (2.10, 2.11, 2.12)].] | 1 mL/kg to 2 mL/kg (with maximum 3 mL/kg) (Maximum single dose: 116 mL)

2.9 Recommended Dosage for Oral or Rectal and Body Cavity Procedures in Pediatric Patients

Recommended Dosage for Radiographic Examination of the GI Tract in Pediatric Patients

- The recommended doses for radiographic examination of the GI tract are shown in Table 11.
- Administer orally or rectally.

Table 11. Recommended Concentrations and Volumes of OMNIPAQUE Injection Based on Age for Radiographic Examination of the GI Tract in Pediatric Patients
Age | Concentration (mg iodine/mL) | Oral Volume | Rectal Volume
Less than 3 months | 180 [Use single-dose containers or 500 mL Pharmacy Bulk Packages [see Dosage and Administration (2.11)].] | 5 mL to 30 mL | May be a larger volume than the volume given orally (up to 300 mL)
3 months to 3 years | 180, 240, or 300 | Up to 60 mL | May be a larger volume than the volume given orally (up to 300 mL)
4 years to 10 years | 180, 240, or 300 | Up to 80 mL | May be a larger volume than the volume given orally (up to 300 mL)
Greater than 10 years | 180, 240, or 300 | Up to 100 mL | May be a larger volume than the volume given orally (up to 300 mL)

Recommended Dosage for CT of the Abdomen and Pelvis in Conjunction with Intravenous Administration of OMNIPAQUE in Pediatric Patients

The recommended oral dose using diluted OMNIPAQUE injection or OMNIPAQUE oral solution and concurrent intravenous dose for CT of the abdomen and pelvis in pediatric patients are shown in Table 12.

Table 12. Recommended Concentrations and Volumes of Diluted OMNIPAQUE Injection or OMNIPAQUE Oral Solution for Oral Administration and Concurrent Intravenous OMNIPAQUE Injection for CT of the Abdomen and Pelvis in Pediatric Patients
Concentration (mg Iodine/mL) | Volume to Administer | Administration Instructions | Maximum Dose by Age or Body Weight
Oral Dose Using Diluted OMNIPAQUE Injection
9 mg Iodine/mL to 21 mg Iodine/mL of Diluted OMNIPAQUE Injection [See Table 13 for dilution instructions of OMNIPAQUE injection] | 180 mL to 750 mL | - Administer the oral dose all at once or over a period of up to 45 minutes if there is difficulty in consuming the required volume. - Use a higher iodine concentration of the diluted product if a smaller volume needs to be administered (see Table 13). | - less than 3 years old: 5 grams iodine - 3 years old to 18 years old: 10 grams iodine
Oral Dose Using OMNIPAQUE Oral Solution
6 mg Iodine/mL or 12 mg Iodine/mL of OMNIPAQUE Oral Solution | 180 mL to 750 mL | Administer the oral dose all at once or over a period of up to 45 minutes if there is difficulty in consuming the required volume. | - less than 3 years old: 5 grams iodine - 3 years old to 18 years old: 10 grams iodine
Intravenous Dose in Conjunction with Oral Administration
240 or 300 [Use single-dose containers, 500 mL Imaging or Pharmacy Bulk Packages, or 150 mL single-dose bottles with an automated contrast injection system or contrast management system [see Dosage and Administration (2.10, 2.11, 2.12)].] | 2 mL/kg body weight (with a range of 1 mL/kg to 2 mL/kg) | Administer up to 60 minutes AFTER consumption of the oral dose. | 3 mL/kg (maximum single dose: 116 mL)

Preparation of Diluted OMNIPAQUE Injection for Oral Administration for CT of the Abdomen and Pelvis in Pediatric Patients

- Prepare the diluted OMNIPAQUE injection in water, carbonated beverage, milk, infant formula, or juice just prior to administration according to Table 13.
- Discard any unused portion after the procedure.

Table 13. Volumes of OMNIPAQUE Injection and Added Liquid to Dilute OMNIPAQUE Injection for Oral Administration for CT of the Abdomen and Pelvis in Pediatric Patients
Concentration of Diluted OMNIPAQUE injection (mg iodine/mL) | Dilution Method 1 |  | Dilution Method 2 |  | Dilution Method 3
Concentration of Diluted OMNIPAQUE injection (mg iodine/mL) | Volume of OMNIPAQUE 240 mg iodine/mL (mL) | Volume of Added Liquid [Use water, carbonated beverage, milk, infant formula, or juice.] (mL) | Volume of OMNIPAQUE 300 mg Iodine/mL (mL) | Volume of Added Liquid (mL) | Volume of OMNIPAQUE 350 mg Iodine/mL (mL) | Volume of Added Liquid (mL)
6 | 25 | 975 | 20 | 980 | 17 | 983
9 | 38 | 962 | 30 | 970 | 26 | 974
12 | 50 | 950 | 40 | 960 | 35 | 965
15 | 63 | 937 | 50 | 950 | 43 | 957
18 | 75 | 925 | 60 | 940 | 52 | 948
21 | 88 | 912 | 70 | 930 | 60 | 940

Recommended Dosage for Voiding Cystourethrography in Pediatric Patients

- Voiding cystourethrography (VCU) can be performed in conjunction with excretory urography [see Dosage and Administration (2.8)].
- The concentration of diluted OMNIPAQUE injection may vary depending upon the patient's size and age and with the technique and equipment used.
- Volume ranges of diluted OMNIPAQUE injection 50 mg iodine/mL and 100 mg iodine/mL are shown in Table 14.
- Dilute OMNIPAQUE injection with Sterile Water for Injection according to Table 15, utilizing aseptic technique, just prior to use.
- Discard any unused portion after the procedure.

Table 14. Volume Ranges of Diluted OMNIPAQUE Injection for VCU in Pediatric Patients
Concentration of Diluted OMNIPAQUE Injection [See Table 15 below for dilution instructions of OMNIPAQUE injection.] (mg iodine/mL) | Volume to Administer
50 | 50 mL to 600 mL by intravesical administration
100 | 50 mL to 300 mL by intravesical administration

Table 15. Volumes of OMNIPAQUE Injection and Sterile Water for Injection to Dilute OMNIPAQUE Injection for VCU in Pediatric Patients
Concentration of Diluted OMNIPAQUE injection (mg iodine/mL) | Dilution Method 1 |  | Dilution Method 2 |  | Dilution Method 3
Concentration of Diluted OMNIPAQUE injection (mg iodine/mL) | Volume of OMNIPAQUE 240 mg Iodine/mL (mL) | Volume of Sterile Water for Injection (mL) | Volume of OMNIPAQUE 300 mg Iodine/mL (mL) | Volume of Sterile Water for Injection (mL) | Volume of OMNIPAQUE 350 mg Iodine/mL (mL) | Volume of Sterile Water for Injection (mL)
50 | 100 | 380 | 100 | 500 | 100 | 600
60 | 100 | 300 | 100 | 400 | 100 | 483
70 | 100 | 243 | 100 | 330 | 100 | 400
80 | 100 | 200 | 100 | 275 | 100 | 338
90 | 100 | 167 | 100 | 233 | 100 | 289
100 | 100 | 140 | 100 | 200 | 100 | 250

2.10 Directions for Use of the 500 mL Bottles of OMNIPAQUE Injection 300 mg Iodine/mL and 350 mg Iodine/mL as Imaging Bulk Package

- OMNIPAQUE injection 300 mg iodine/mL and OMNIPAQUE injection 350 mg iodine/mL in 500 mL bottles may be used as an Imaging Bulk Package (IBP) for intravenous use [see Dosage and Administration (2.4, 2.8)].
- When used as an IBP, check the appropriate box on the container label to indicate that the selected container is to be utilized as an Imaging Bulk Package. This container is for use only with an automated contrast injection system, contrast management system, or contrast media transfer set approved or cleared for use with this contrast agent in this IBP. See device labeling for information on devices indicated for use with this IBP and techniques to help assure safe use.
- Use the OMNIPAQUE IBP and 0.9% Sodium Chloride Injection USP in a room designated for radiological procedures that involve administration of a contrast agent.
- Using aseptic technique, penetrate the container closure only one time with a suitable sterile component of the automated contrast injection system, contrast management system, or contrast media transfer set cleared for use with the OMNIPAQUE IBP.
- If 0.9% Sodium Chloride Injection USP is used with the OMNIPAQUE IBP, prepare the 0.9% Sodium Chloride Injection USP sterile port in accordance with the dosage and administration section of its approved prescribing information and affix the saline tag provided with the OMNIPAQUE IBP on the 0.9% Sodium Chloride Injection USP container.
- Once the OMNIPAQUE IBP and 0.9% Sodium Chloride Injection containers are punctured, do not remove them from the work area during the entire period of use. Maintain the OMNIPAQUE IBP in an inverted position such that container contents are in continuous contact with the dispensing set.
- After the container closure is punctured, if the integrity of the OMNIPAQUE IBP, the 0.9% Sodium Chloride Injection, and the delivery system cannot be assured through direct continuous supervision, discard the IBP, 0.9% Sodium Chloride Injection USP, and all associated disposables for the contrast media transfer set.
- A maximum time from initial puncture is 8 hours. Discard any unused portion.

2.11 Directions for Use of the 500 mL Bottles of OMNIPAQUE Injection 300 mg Iodine/mL and 350 mg Iodine/mL as Pharmacy Bulk Package

- OMNIPAQUE injection 300 mg iodine/mL and OMNIPAQUE injection 350 mg iodine/mL in 500 mL bottles contain many single doses and may be used as a Pharmacy Bulk Package (PBP).
- When used as a PBP, check the appropriate box on the container label to indicate that the selected container is to be utilized as a Pharmacy Bulk Package. This container is not for direct infusion; it is for use in pharmacy admixture service to dispense aliquots using a suitable dispensing set under a laminar flow hood or equivalent clean air compounding area using aseptic technique.
- Penetrate the container closure only one time, utilizing a suitable transfer device and aseptic technique.
- The withdrawal of container contents should be accomplished without delay. However, should this not be possible, a maximum time of 8 hours from initial closure entry is permitted to complete fluid transfer operations.
- Do not remove the container from the aseptic area during the entire 8-hour period.
- The temperature of the container should not exceed 37°C (98.6°F), after the closure has been entered.
- Discard any unused portion after 8 hours from the initial closure entry.

2.12 Directions for Use of the 150 mL Bottles of OMNIPAQUE Injection 300 mg Iodine/mL and 350 mg Iodine/mL with an Automated Contrast Injection System or Contrast Management System

- OMNIPAQUE injection 300 mg iodine/mL and OMNIPAQUE injection 350 mg iodine/mL in 150 mL bottles may be used with a contrast media management system cleared for use with OMNIPAQUE injection 300 mg iodine/mL and 350 mg iodine/mL in 150 mL bottles.
- See device labeling for information on device indications, instructions for use, and techniques to help assure safe use.
- Using aseptic technique, penetrate the container closure only one time with a suitable sterile component of the contrast media management system cleared for use with OMNIPAQUE 300 mg iodine/mL and 350 mg iodine/mL in 150 mL bottles.
- Once the container is punctured, do not remove the bottle from the work area during the entire period of use.
- Maximum use time is 4 hours after initial puncture.
- Each bottle is for one procedure only. Discard unused portion.

3 DOSAGE FORMS AND STRENGTHS

Injection and Oral Solution: Colorless to pale yellow solution available in the following presentations:

Dosage Form | Concentration (mg of iodine/mL) | Package Size | Package Type
Injection | 140 | 50 mL | Single-Dose Bottle
Injection | 180 | 10 mL | Single-Dose Vial
Injection | 240 | 10 mL and 20 mL | Single-Dose Vial
Injection | 240 | 50 mL and 100 mL | Sigle-Dose Bottle
Injection | 300 | 10 mL | Single-Dose Vial
Injection | 300 | 30 mL, 50 mL, 100 mL, 125 mL, and 150 mL | Single-Dose Bottle
Injection | 300 | 500 mL [OMNIPAQUE injection 300 mg iodine/mL and OMNIPAQUE injection 350 mg iodine/mL in bottles of 500 mL can be used as either an Imaging Bulk Package or a Pharmacy Bulk Package [see Dosage and Administration (2.10, 2.11)].] | Imaging or Pharmacy Bulk Package
Injection | 350 | 50 mL, 75 mL, 100 mL, 125 mL, 150 mL, and 200 mL | Single-Dose Bottle
Injection | 350 | 500 mL | Imaging or Pharmacy Bulk Package
Oral Solution | 9 | 500 mL | Single-Dose Bottle
Oral Solution | 12 | 500 mL | Single-Dose Bottle

4 CONTRAINDICATIONS

OMNIPAQUE for hysterosalpingography is contraindicated during pregnancy or suspected pregnancy, menstruation or when menstruation is imminent, within 6 months after termination of pregnancy, within 30 days after conization or curettage, when signs of infection are present in any portion of the genital tract including the external genitalia, and when reproductive tract neoplasia is known or suspected because of the risk of peritoneal spread of neoplasm.

5 WARNINGS AND PRECAUTIONS

5.1 Risks Associated with Intrathecal Administration of OMNIPAQUE Injection 140 mg Iodine/mL and 350 mg Iodine/mL

Use only the iodine concentrations and presentations recommended for intrathecal procedures [see Dosage and Administration (2.2, 2.8)]. Intrathecal administration of OMNIPAQUE of a wrong iodine concentration, even if inadvertent, can cause death, convulsions, seizures, cerebral hemorrhage, coma, paralysis, arachnoiditis, acute renal failure, cardiac arrest, rhabdomyolysis, hyperthermia, and brain edema.

5.2 Risks Associated with Parenteral Administration of OMNIPAQUE Oral Solution

Adverse reactions such as hemolysis may occur if OMNIPAQUE oral solution is administered intravenously or intraarterially due to low osmolality [see Description (11)]. OMNIPAQUE oral solution is for oral use only.

5.3 Hypersensitivity Reactions

OMNIPAQUE can cause life-threatening or fatal hypersensitivity reactions including anaphylaxis. Manifestations include respiratory arrest, laryngospasm, bronchospasm, angioedema, and shock. Most severe reactions develop shortly after the start of the injection (within 1 to 3 minutes), but delayed reactions can also occur. There is an increased risk in patients with a history of a previous reaction to contrast agent and known allergic disorders (i.e., bronchial asthma, drug, or food allergies) or other hypersensitivities. Premedication with antihistamines or corticosteroids does not prevent serious life-threatening reactions but may reduce both their incidence and severity.

Obtain a history of allergy, hypersensitivity, or hypersensitivity reactions to iodinated contrast agents and always have emergency resuscitation equipment and trained personnel available prior to OMNIPAQUE administration. Monitor all patients for hypersensitivity reactions.

5.4 Acute Kidney Injury

Acute kidney injury, including renal failure, may occur after parenteral administration of OMNIPAQUE. Risk factors include: pre-existing renal impairment, dehydration, diabetes mellitus, congestive heart failure, advanced vascular disease, elderly age, concomitant use of nephrotoxic or diuretic medications, multiple myeloma/paraproteinaceous diseases, repetitive and/or large doses of an iodinated contrast agent.

Use the lowest necessary dose of OMNIPAQUE in patients with renal impairment. Adequately hydrate patients prior to and following parenteral administration of OMNIPAQUE. Do not use laxatives, diuretics, or preparatory dehydration prior to OMNIPAQUE administration.

5.5 Cardiovascular Adverse Reactions

Life-threatening or fatal cardiovascular reactions including hypotension, shock, cardiac arrest have occurred with the parenteral administration of OMNIPAQUE. Most deaths occur during injection or five to ten minutes later, with cardiovascular disease as the main aggravating factor. Cardiac decompensation, serious arrhythmias, and myocardial ischemia or infarction can occur during coronary arteriography and ventriculography.

Based on clinical literature, reported deaths from the administration of iodinated contrast agents range from 6.6 per million (0.00066%) to 1 in 10,000 (0.01%). Use the lowest necessary dose of OMNIPAQUE in patients with congestive heart failure and always have emergency resuscitation equipment and trained personnel available. Monitor all patients for severe cardiovascular reactions.

5.6 Thromboembolic Events

Serious, rarely fatal, thromboembolic events causing myocardial infarction and stroke can occur during angiocardiography procedures with iodinated contrast agents including OMNIPAQUE. During these procedures, increased thrombosis and activation of the complement system occurs. Risk factors for thromboembolic events include: length of procedure, catheter and syringe material, underlying disease state, and concomitant medications.

To minimize thromboembolic events, use meticulous angiographic techniques, and minimize the length of the procedure. Avoid blood remaining in contact with syringes containing OMNIPAQUE, which increases the risk of clotting. Avoid angiocardiography in patients with homocystinuria because of the risk of inducing thrombosis and embolism.

5.7 Extravasation and Injection Site Reactions

Extravasation of OMNIPAQUE during intravenous or intra-arterial injection may cause tissue necrosis and/or compartment syndrome, particularly in patients with severe arterial or venous disease. Ensure intravenous or intra-arterial placement of catheters prior to injection. Monitor patients for extravasation and advise patients to seek medical care for progression of symptoms.

5.8 Thyroid Storm in Patients with Hyperthyroidism

Thyroid storm has occurred after the intravenous or intra-arterial use of iodinated contrast agents in patients with hyperthyroidism, or with an autonomously functioning thyroid nodule. Evaluate the risk in such patients before use of OMNIPAQUE.

5.9 Thyroid Dysfunction in Pediatric Patients 0 to 3 Years of Age

Thyroid dysfunction characterized by hypothyroidism or transient thyroid suppression has been reported after both single exposure and multiple exposures to iodinated contrast media (ICM) in pediatric patients 0 to 3 years of age.

Younger age, very low birth weight, prematurity, underlying medical conditions affecting thyroid function, admission to neonatal or pediatric intensive care units, and congenital cardiac conditions are associated with an increased risk of hypothyroidism after ICM exposure. Pediatric patients with congenital cardiac conditions may be at the greatest risk given that they often require high doses of contrast during invasive cardiac procedures.

An underactive thyroid during early life may be harmful for cognitive and neurological development and may require thyroid hormone replacement therapy. After exposure to ICM, individualize thyroid function monitoring based on underlying risk factors, especially in term and preterm neonates.

5.10 Hypertensive Crisis in Patients with Pheochromocytoma

Hypertensive crisis has occurred after the use of iodinated contrast agents in patient with pheochromocytoma. Monitor patients when administering OMNIPAQUE intravenously or intra-arterially if pheochromocytoma or catecholamine-secreting paragangliomas are suspected. Inject the minimum amount of contrast necessary, assess the blood pressure throughout the procedure, and have measures for treatment of a hypertensive crisis readily available.

5.11 Sickle Cell Crisis in Patients with Sickle Cell Disease

Iodinated contrast agents when administered intravenously or intra-arterially may promote sickling in individuals who are homozygous for sickle cell disease. Hydrate patients prior to and following OMNIPAQUE administration and use OMNIPAQUE only if the necessary imaging information cannot be obtained with alternative imaging modalities.

5.12 Severe Cutaneous Adverse Reactions

Severe cutaneous adverse reactions (SCAR) may develop from 1 hour to several weeks after intravenous or intra-arterial contrast agent administration. These reactions include Stevens-Johnson syndrome and toxic epidermal necrolysis (SJS/TEN), acute generalized exanthematous pustulosis (AGEP) and drug reaction with eosinophilia and systemic symptoms (DRESS). Reaction severity may increase and time to onset may decrease with repeat administration of contrast agents; prophylactic medications may not prevent or mitigate severe cutaneous adverse reactions. Avoid administering OMNIPAQUE to patients with a history of a severe cutaneous adverse reaction to OMNIPAQUE.

5.13 Interference with Laboratory Test

OMNIPAQUE can interfere with protein-bound iodine test [see Drug Interactions (7.2)].

5.14 Increased Risk of Seizures with Intrathecal Procedures

Focal and generalized motor seizures have been reported after intrathecal use of iodinated contrast agents. In several of the cases, higher than recommended doses were administered.

Use of medications that may lower the seizure threshold (phenothiazine derivatives, including those used for their antihistaminic properties; tricyclic antidepressants; MAO inhibitors; CNS stimulants; analeptics; antipsychotic agents) should be carefully evaluated. Consider discontinuing these agents at least 48 hours before and for at least 24 hours following intrathecal administration of OMNIPAQUE.

6 ADVERSE REACTIONS

The following clinically significant adverse reactions are described elsewhere in the labeling:

- Risks Associated with Intrathecal Administration of OMNIPAQUE Injection 140 mg Iodine/mL and 350 mg Iodine/mL [see Warnings and Precautions (5.1)]
- Risks Associated with Parenteral Administration of OMNIPAQUE Oral Solution [see Warnings and Precautions (5.2)]
- Hypersensitivity Reactions [see Warnings and Precautions (5.3)]
- Acute Kidney Injury [see Warnings and Precautions (5.4)]
- Cardiovascular Adverse Reactions [see Warnings and Precautions (5.5)]
- Thromboembolic Events [see Warnings and Precautions (5.6)]
- Thyroid Dysfunction in Pediatric Patients 0 to 3 Years of Age [see Warnings and Precautions (5.9)]
- Severe Cutaneous Adverse Reactions [see Warnings and Precautions (5.12)]

6.1 Clinical Trials Experience

Because clinical trials are conducted under widely varying conditions, adverse reaction rates observed in the clinical trials of a drug cannot be directly compared to rates in the clinical trials of another drug and may not reflect the rates observed in practice.

Intrathecal Administration

Adults

Adverse reactions (≥1%) in 1,531 adult patients following intrathecal administration of OMNIPAQUE in clinical trials are presented in Table 16.

Table 16. Adverse Reactions (≥1%) in in Adult Patients Following Intrathecal Administration of OMNIPAQUE in Clinical Trials
System Organ Class | Adverse Reaction | Incidence N=1,531
Nervous system disorders | Headaches | 18%
Musculoskeletal and connective tissue disorders | Pain including backache, neckache, stiffness, neuralgia | 8%
Gastrointestinal disorders | Nausea | 6%
Gastrointestinal disorders | Vomiting | 3%
Nervous System disorders | Dizziness | 2%

Other adverse reactions (<1%) were:

Ear and labyrinth disorders: tinnitus, vertigo
Eye disorders: photophobia
General disorders and administration site conditions: sensation of heat
Metabolism and nutrition disorders: loss of appetite
Musculoskeletal and connective tissue disorders: feeling of heaviness
Nervous system disorders: drowsiness, hypertonia, neuralgia, neurological changes, paresthesia, syncope
Renal and urinary disorders: difficulty in micturition
Skin and subcutaneous tissue disorders: sweating
Vascular disorders: hypertension, hypotension

Pediatric Patients

The adverse reactions reported in pediatric patients following intrathecal administration of OMNIPAQUE were generally similar to those reported in adults. A total of 152 pediatric patients were administered OMNIPAQUE 180 mg iodine/mL intrathecally by lumbar puncture for pediatric myelography in clinical trials. Adverse reactions (≥1%) are presented in Table 17.

Table 17. Adverse Reactions (≥1%) in Pediatric Patients Following Intrathecal Administration of OMNIPAQUE 180 mg iodine/mL by Lumbar Puncture for Myelography in Clinical Trials
System Organ Class | Adverse Reaction | Incidence N=152
Nervous system disorders | Headache | 9%
Gastrointestinal disorders | Vomiting | 6%
Musculoskeletal and connective tissue disorders | Backache | 1.3%

Other adverse reactions (<1%) were:

Gastrointestinal disorders: stomachache
General disorders and administration site conditions: fever
Nervous system disorders: neurological changes
Psychiatric disorders: visual hallucination
Skin and subcutaneous tissue disorders: hives

Intra-arterial or Intravenous Administration

Adults

Adverse reactions (≥1%) in 1,485 adult patients following intra-arterial or intravenous administration of OMNIPAQUE in clinical trials are presented in Table 18.

Table 18. Adverse Reactions (≥1%) in Adult Patients Following Intra-arterial or Intravenous Administration of OMNIPAQUE in Clinical Trials
System Organ Class | Adverse Reaction | Incidence (N=1,485)
Cardiac disorders | Arrhythmias including PVCs and PACs | 2%
Nervous system disorders | Pain | 3%
Nervous system disorders | Vision abnormalities including blurred vision and photomas | 2%
Nervous system disorders | Taste perversion | 1%
Gastrointestinal disorders | Nausea | 2%

Other adverse reactions (<1%) were:

Cardiac disorders: hypotension, cardiac failure, asystole, bradycardia, tachycardia, vasovagal reaction
Respiratory, thoracic and mediastinal disorders: dyspnea, rhinitis, coughing, laryngitis
Gastrointestinal disorders: vomiting, diarrhea, dyspepsia, cramp, dry mouth
General disorders and administration site conditions: fever, shivering
Nervous system disorders: cerebral infarction, convulsion, hemiparesis, motor and speech dysfunction, nystagmus, paresthesia, somnolence, transient ischemic attack, vertigo including dizziness and lightheadedness
Musculoskeletal and connective tissue disorders: still neck
Skin and subcutaneous tissue disorders: urticaria, abscess, pruritus, purpura
Psychiatric disorders: anxiety, syncope

Pediatric Patients

Adverse reactions reported in pediatric patients following intra-arterial or intravenous administration of OMNIPAQUE were generally similar in quality and frequency to those reported in adults. A total of 391 pediatric patients in clinical trials were administered OMNIPAQUE 240 mg iodine/mL, 300 mg iodine/mL, or 350 mg iodine/mL by intra-arterial or intravenous injection for pediatric cardiac ventriculography, excretory urography, and CT head imaging.

Adverse reactions (≥1%) were vomiting (2%) and nausea (1%).

Other adverse reactions (<1%) were:

Cardiac disorders: Ventricular tachycardia, 2:1 heart block, hypertension, anemia
General disorders and administration site conditions: Pain, fever
Nervous system disorders: Convulsion, taste abnormality
Respiratory, thoracic and mediastinal disorders: Congestion, apnea
Endocrine disorders: Hypoglycemia
Skin and subcutaneous tissue disorders: Rash

Oral or Rectal Administration for Examination of the Gastrointestinal Tract

Adults

A total of 54 adult patients were administered undiluted OMNIPAQUE 350 mg iodine/mL by oral route for radiographic examination of the gastrointestinal tract in clinical trials. Adverse reactions (≥1%) are presented in Table 19.

Table 19. Adverse Reactions (≥1%) in Adult Patients Following Oral Administration of Undiluted OMNIPAQUE 350 mg Iodine/mL in Clinical Trials
System Organ Class | Adverse Reaction | Incidence N=54
Gastrointestinal disorders | Diarrhea | 42%
Gastrointestinal disorders | Nausea | 15%
Gastrointestinal disorders | Vomiting | 11%
Gastrointestinal disorders | Abdominal Pain | 7%
Gastrointestinal disorders | Flatulence | 2%
Nervous system disorders | Headache | 2%

Pediatrics Patients

A total of 58 pediatric patients were administered OMNIPAQUE by oral or rectal administration in clinical trials. Adverse reactions (≥1%) are presented in Table 20.

Table 20. Adverse Reactions (≥1%) in Pediatric Patients Following Oral or Rectal Administration of OMNIPAQUE in Clinical Trials
System Organ Class | Adverse Reaction | Incidence N=58
Gastrointestinal disorders | Diarrhea | 36%
Gastrointestinal disorders | Vomiting | 9%
Gastrointestinal disorders | Nausea | 5%
Gastrointestinal disorders | Abdominal pain | 2%
General disorders and administration site conditions | Fever | 5%
Skin and subcutaneous tissue disorders | Urticaria | 2%
Vascular disorders | Hypotension | 2%

Oral Administration for CT of the Abdomen in Conjunction with Intravenous Administration

Adults

A total of 44 adult patients received diluted OMNIPAQUE (4-9 mg iodine/mL) by oral route in conjunction with intravenously injected OMNIPAQUE 300 mg iodine/mL for CT examination of the abdomen in clinical trials. Adverse reactions (≥1%) were limited to a single report of vomiting (2.3%).

Pediatric Patients

A total of 69 pediatric patients received diluted OMNIPAQUE (9-29 mg iodine/mL) by oral route in conjunction with intravenously administered OMNIPAQUE 240 mg iodine/mL or OMNIPAQUE 300 mg iodine/mL for CT examination of the abdomen in clinical trials. Adverse reactions (≥1%) were limited to a single report of vomiting (1.4%).

Intraarticular Administration

Arthrography in Adults

A total of 285 adult patients received OMNIPAQUE 240 mg iodine/mL, 300 mg iodine/mL, or 350 mg iodine/mL for various body cavity examinations in clinical trials. The most frequent adverse reactions (≥1%) were administration site pain (26%) and swelling (22%) in arthrography. Patients also experienced heat (7%).

Body Cavity Use

VCU in Pediatric Patients

No new adverse reactions associated with the use of OMNIPAQUE for VCU procedures were reported in 51 pediatric patients studied.

6.2 Post-marketing Experience

The following adverse reactions have been identified during post-approval use of OMNIPAQUE. Because these reactions are reported voluntarily from a population of uncertain size, it is not always possible to reliably estimate their frequency or establish a causal relationship to drug exposure.

General

Immune system disorders: Hypersensitivity reactions, anaphylactic or anaphylactoid reactions, anaphylactic or anaphylactoid shock including life-threatening or fatal anaphylaxis

General disorders and administration site conditions: Pyrexia, chills, pain and discomfort, asthenia, administration site conditions including extravasation

Intrathecal Administration

Nervous system disorders: Meningism, aseptic meningitis, seizures or status epilepticus, disorientation, coma, depressed or loss of consciousness, transient contrast-induced toxic encephalopathy (including amnesia, hallucination, paralysis, paresis, speech disorder, aphasia, dysarthria), restlessness, tremors, hypoesthesia

Musculoskeletal and connective tissue disorders: Pain, muscle spasms or spasticity

Psychiatric disorders: Confusional state, agitation, anxiety

Eye disorders: Transient visual impairment including cortical blindness

Renal and urinary disorders: Acute kidney injury

Intra-arterial or Intravenous Administration

Cardiac disorders: Severe cardiac complications (including cardiac arrest, cardiopulmonary arrest), shock, peripheral vasodilatation, palpitations, vasospasm including spasm of coronary arteries, myocardial infarction, syncope, cyanosis, pallor, flushing, chest pain

Vascular disorders: Vasospasm and thrombophlebitis following intravenous injection

Blood and lymphatic system disorders: Neutropenia

Nervous system disorders: Disorientation, coma, depressed or loss of consciousness, transient contrast-induced toxic encephalopathy (including amnesia, hallucination, paralysis, paresis, speech disorder, aphasia, dysarthria), restlessness, tremors, hypoesthesia

Psychiatric disorders: Confusional state, agitation

Eye disorders: Eye irritation or itchiness, periorbital edema, ocular or conjunctival hyperemia, lacrimation

Renal and urinary disorders: Acute kidney injury, toxic nephropathy (CIN), transient proteinuria, oliguria or anuria, increased serum creatinine

Gastrointestinal disorders: Abdominal pain, pancreatitis aggravated, salivary gland enlargement

Endocrine disorders: Hyperthyroidism, hypothyroidism

Respiratory, thoracic and mediastinal disorders: Respiratory distress, respiratory failure, pulmonary edema, bronchospasm, laryngospasm, throat irritation, throat tightness, laryngeal edema, wheezing, chest discomfort, asthmatic attack

Skin and subcutaneous tissue disorders: Contrast media reactions range from mild (e.g., pleomorphic rashes, drug eruption, erythema and skin discoloration, blisters, hyperhidrosis, angioedema, localized areas of edema) to severe (e.g., Stevens-Johnson syndrome and toxic epidermal necrolysis [SJS/TEN], bullous or exfoliative dermatitis, acute generalized exanthematous pustulosis [AGEP] and drug reaction with eosinophilia and systemic symptoms [DRESS])

Oral Administration

Gastrointestinal disorders: Dysphagia, abdominal pain

Body Cavity Administration

Gastrointestinal disorders: Pancreatitis

Musculoskeletal and connective tissue disorders: Arthritis (arthrography)

Hysterosalpingography: Injection of OMNIPAQUE for hysterosalpingography is associated with immediate, transient pain. Monitor injection pressure and volume instilled to minimize pain and to avoid disruptive distention of the uterus and fallopian tubes. Fluoroscopic monitoring is recommended.

Nervous system disorders: Pain (49%), somnolence and fever each with an individual incidence of 3%

Gastrointestinal disorders: Nausea (3%)

7 DRUG INTERACTIONS

7.1 Drug-Drug Interactions

Metformin

In patients with renal impairment, metformin can cause lactic acidosis. Iodinated contrast agents appear to increase the risk of metformin-induced lactic acidosis, possibly as a result of worsening renal function. Stop metformin at the time of, or prior to, OMNIPAQUE administration in patients with an eGFR between 30 and 60 mL/min/1.73 m^2; in patients with a history of hepatic impairment, alcoholism or heart failure; or in patients who will be administered intra-arterial iodinated contrast. Re-evaluate eGFR 48 hours after the imaging procedure, and reinstitute metformin only after renal function is stable.

Radioactive Iodine

OMNIPAQUE may interfere with thyroid uptake of radioactive iodine (I-131 and I-123) and decrease therapeutic and diagnostic efficacy. Avoid thyroid therapy or testing for up to 6 weeks post OMNIPAQUE.

7.2 Drug-Laboratory Test Interactions

Protein-Bound Iodine Test

Iodinated contrast agents, including OMNIPAQUE, will temporarily increase protein-bound iodine in blood. Do not perform protein-bound iodine test for at least 16 days following administration of OMNIPAQUE. However, thyroid function tests that do not depend on iodine estimation, e.g., T3 resin uptake or direct thyroxine assays, are not affected.

8 USE IN SPECIFIC POPULATIONS

8.1 Pregnancy

Risk Summary

Hysterosalpingography is contraindicated in pregnant women due to the potential risk to the fetus from an intrauterine procedure [see Contraindications (4)]. There are no data with iohexol use in pregnant women to inform any drug-associated risks. Iohexol crosses the placenta and reaches fetal tissues in small amounts (see Data). In animal reproduction studies, no developmental toxicity occurred with intravenous iohexol administration to rats and rabbits at doses up to 0.4 (rat) and 0.5 (rabbit) times the maximum recommended human intravenous dose (see Data).

The estimated background risk of major birth defects and miscarriage for the indicated population is unknown. All pregnancies have a background risk of birth defect, loss or other adverse outcomes. In the U.S. general population, the estimated background risk of major birth defects and miscarriage in clinically recognized pregnancies is 2 to 4% and 15 to 20%, respectively.

Data

Human Data

Literature reports show that intravenously administered iohexol crosses the placenta and is visualized in the digestive tract of exposed infants after birth.

Animal Data

Iohexol was neither embryotoxic nor teratogenic in either rats or rabbits at the following dose levels tested: 1.0, 2.0, 4.0 g iodine/kg in rats, administered intravenously to 3 groups of 25 dams once daily during days 6 through 15 of pregnancy; 0.3, 1.0, 2.5 g iodine/kg in rabbits, administered intravenously to 3 groups of 18 rabbits dosed once a day during days 6 through 18 of pregnancy.

8.2 Lactation

Risk Summary

Published literature reports that breast feeding after intravenous iohexol administration to the mother would result in the infant receiving an oral dose of approximately 0.7% of the maternal intravenous dose; however, lactation studies have not been conducted with oral, intrathecal, or intracavity administration of iohexol. There is no information on the effects of the drug on the breastfed infant or on milk production. Iodinated contrast agents are excreted unchanged in human milk in very low amounts with poor absorption from the gastrointestinal tract of a breastfed infant. Exposure to iohexol to a breastfed infant can be minimized by temporary discontinuation of breastfeeding (see Clinical Considerations). The developmental and health benefits of breastfeeding should be considered along with the mother's clinical need for OMNIPAQUE and any potential adverse effects on the breastfed infant from OMNIPAQUE or from the underlying maternal condition.

Clinical Considerations

Interruption of breastfeeding after exposure to iodinated contrast agents is not necessary because the potential exposure of the breastfed infant to iodine is small. However, a lactating woman may consider interrupting breastfeeding and pumping and discarding breast milk for 10 hours (approximately 5 elimination half-lives) after OMNIPAQUE administration to minimize drug exposure to a breastfed infant.

8.4 Pediatric Use

Intrathecal Use

The safety and effectiveness of OMNIPAQUE have been established in pediatric patients aged 2 weeks and older for myelography and CT myelography (lumbar, thoracic, cervical, total columnar) and for CT cisternography. Use of OMNIPAQUE is supported by controlled clinical studies in adults for myelography, in addition to clinical studies in pediatric patients undergoing myelography.

The safety and effectiveness of OMNIPAQUE have not been established for intrathecal use in pediatric patients less than 2 weeks of age.

The safety and effectiveness of OMNIPAQUE for CT cerebral ventriculography have not been established in pediatric patients.

Intra-arterial or Intravenous Use

Cardiac Ventriculography, Aortography, and Pulmonary Angiography

The safety and effectiveness of OMNIPAQUE have been established in pediatric patients from birth to 17 years of age for cardiac ventriculography, aortography, and pulmonary angiography. Use of OMNIPAQUE is supported by controlled clinical studies in adults for cardiac ventriculography and aortography, in addition to controlled clinical studies in pediatric patients undergoing cardiac ventriculography, including aortography.

Excretory Urography

The safety and effectiveness of OMNIPQUE have been established in pediatric patients from birth to 17 years of age for excretory urography. Use of OMNIPAQUE is supported by controlled clinical studies in adults for urography, in addition to controlled clinical studies in pediatric patients undergoing urography and clinical safety data in pediatric patients down to birth.

CT of the Head and Body

The safety and effectiveness of OMNIPAQUE have been established in pediatric patients from birth to 17 years of age for CT imaging of the head and body. Use of OMNIPAQUE is supported by controlled clinical studies in adults for head and body CT, in addition to clinical studies in pediatric patients undergoing head CT and in 69 pediatric patients undergoing CT of the abdomen after oral administration of diluted OMNIPAQUE plus intravenous administration of OMNIPAQUE.

Selective Coronary Arteriography, Cerebral and Peripheral Arteriography, Intra-arterial Digital Subtraction Angiography, Peripheral Venography, and Intravenous Digital Subtraction Angiography

The safety and effectiveness of OMNIPAQUE have not been established in pediatric patients for selective coronary arteriography, cerebral or peripheral arteriography, intra-arterial digital subtraction angiography, peripheral venography, and intravenous digital subtraction angiography.

Oral or Rectal Use

Examination of the GI Tract

The safety and effectiveness of OMNIPAQUE have been established in pediatric patients, from birth to 17 years of age for examination of the GI tract. Use of OMNIPAQUE is supported by controlled studies in adults for examination of the GI tract, in addition to clinical studies in pediatric patients undergoing examination of the GI tract.

CT of the Abdomen and Pelvis in Conjunction with Intravenous Use

The safety and effectiveness of OMNIPAQUE for CT of the abdomen and pelvis have been established in pediatric patients from birth to 17 years of age. Use is supported by clinical trials in adults, in addition to clinical studies in 69 pediatric patients undergoing CT of the abdomen.

Intraarticular Use

The safety and effectiveness of OMNIPAQUE have not been established in pediatric patients for arthrography.

Body Cavity Use

Voiding Cystourethrography

OMNIPAQUE is indicated for use in pediatric patients from birth to 17 years of age for voiding cystourethrography (VCU). Use for voiding cystourethrography is supported by clinical studies in 51 pediatric patients undergoing VCU.

ERCP, Herniography, and Hysterosalpingography

The safety and effectiveness of OMNIPAQUE have not been established in pediatric patients for ERCP, herniography, or hysterosalpingography.

In general, the frequency of adverse reactions in pediatric patients was similar to that seen in adults [see Adverse Reactions (6.1)]. Pediatric patients at higher risk of experiencing adverse events during contrast-medium administration may include those having asthma, a sensitivity to medication and/or allergens, congestive heart failure, a serum creatinine greater than 1.5 mg/dL or those less than 12 months of age.

Thyroid function tests indicative of thyroid dysfunction, characterized by hypothyroidism or transient thyroid suppression have been reported following iodinated contrast media administration in pediatric patients, including term and preterm neonates. Some patients were treated for hypothyroidism. After exposure to iodinated contrast media, individualize thyroid function monitoring in pediatric patients 0 to 3 years of age based on underlying risk factors, especially in term and preterm neonates [see Warnings and Precautions (5.9) and Adverse Reactions (6.2)].

8.5 Geriatric Use

In clinical studies of OMNIPAQUE for CT of the head and body, 52 (17%) of patients were 70 and over. No overall differences in safety were observed between these patients and younger patients. Other reported clinical experience has not identified differences in safety and effectiveness between the elderly and younger patients.

Iohexol is substantially excreted by the kidney, and the risk of adverse reactions to iohexol may be greater in patients with impaired renal function. Because elderly patients are more likely to have decreased renal function, care should be taken in dose selection, and it may be useful to monitor renal function.

8.6 Renal Impairment

The clearance of iohexol decreases with increasing degree of renal impairment and results in delayed opacification of the urinary system. In addition, preexisting renal impairment increases the risk for acute kidney injury [see Warnings and Precautions (5.4)]. Iohexol can be removed by dialysis.

10 OVERDOSAGE

The adverse effects of overdosage in intra-arterial or intravenous administration are life-threatening and affect mainly the pulmonary and cardiovascular systems. The symptoms include: cyanosis, bradycardia, acidosis, pulmonary hemorrhage, convulsions, coma, and cardiac arrest. Treatment of an overdosage is directed toward the support of all vital functions, and prompt institution of symptomatic therapy. Iohexol can be dialyzed.

11 DESCRIPTION

Iohexol is a nonionic radiographic contrast agent available as:

- OMNIPAQUE (iohexol) injection for intrathecal, intra-arterial, intravenous, oral, rectal, intraarticular, and body cavity use
- OMNIPAQUE (iohexol) oral solution for oral use

The chemical name of iohexol is Bis(2,3-dihydroxypropyl)-5-[N-(2,3-dihydroxypropyl)-acetamido]-2,4,6- triiodoisophthalamide with a molecular weight of 821.14 (iodine content 46.36%). Iohexol has the following structural formula:

OMNIPAQUE injection is a sterile, pyrogen-free, colorless to pale yellow solution available in five concentrations of iodine:

- OMNIPAQUE 140 mg iodine/mL: Each mL contains 302 mg iohexol (providing 140 mg organically bound iodine) and the following inactive ingredients: 0.1 mg edetate calcium disodium and 1.21 mg tromethamine.
- OMNIPAQUE 180 mg iodine/mL: Each mL contains 388 mg iohexol (providing 180 mg organically bound iodine) and the following inactive ingredients: 0.1 mg edetate calcium disodium and 1.21 mg tromethamine.
- OMNIPAQUE 240 mg iodine/mL: Each mL contains 518 mg iohexol (providing 240 mg organically bound iodine) and the following inactive ingredients: 0.1 mg edetate calcium disodium and 1.21 mg tromethamine.
- OMNIPAQUE 300 mg iodine/mL: Each mL contains 647 mg iohexol (providing 300 mg organically bound iodine) and the following inactive ingredients: 0.1 mg edetate calcium disodium and 1.21 mg tromethamine.
- OMNIPAQUE 350 mg iodine/mL: Each mL contains 755 mg iohexol (providing 350 mg organically bound iodine) and the following inactive ingredients: 0.1 mg edetate calcium disodium and 1.21 mg tromethamine.

OMNIPAQUE oral solution is a sterile, pyrogen-free, colorless to pale yellow solution available in two concentrations of iodine:

- OMNIPAQUE oral solution 9 mg iodine/mL: Each mL contains 19 mg iohexol (providing 9 mg organically bound iodine) and the following inactive ingredients: 0.1 mg edetate calcium disodium and 1.21 mg tromethamine.
- OMNIPAQUE oral solution 12 mg iodine/mL: Each mL contains 26 mg iohexol (providing 12 mg organically bound iodine) and the following inactive ingredients: 0.1 mg edetate calcium disodium and 1.21 mg tromethamine.

The pH is adjusted between 6.8 and 7.7 with hydrochloric acid or sodium hydroxide. OMNIPAQUE injection and OMNIPAQUE oral solution contain no preservatives and no ingredient made from a gluten-containing grain (wheat, barley, or rye).

OMNIPAQUE injection and OMNIPAQUE oral solution have the following physical properties:

Table 21. Physicochemical Properties of OMNIPAQUE
Dosage Form | Concentration (mg iodine/mL) | Osmolality [By vapor-pressure osmometry.] (mOsmol/kg water) | Absolute Viscosity (cP) |  | Specific Gravity
Dosage Form | Concentration (mg iodine/mL) | Osmolality [By vapor-pressure osmometry.] (mOsmol/kg water) | 20°C | 37°C | 37°C
Injection | 140 | 322 | 2.3 | 1.5 | 1.164
Injection | 180 | 408 | 3.1 | 2.0 | 1.209
Injection | 240 | 520 | 5.8 | 3.4 | 1.280
Injection | 300 | 672 | 11.8 | 6.3 | 1.349
Injection | 350 | 844 | 20.4 | 10.4 | 1.406
Oral solution | 9 | 38 | 1.1 | 0.8 | 1.011
Oral solution | 12 | 45 | 1.1 | 0.8 | 1.014

OMNIPAQUE injection has osmolalities from approximately 1.1 to 3 times that of plasma (285 mOsmol/kg water) or cerebrospinal fluid (301 mOsmol/kg water) as shown in the above table and are hypertonic .

OMNIPAQUE oral solution is hypotonic.

12 CLINICAL PHARMACOLOGY

12.1 Mechanism of Action

The iodine atoms in iohexol provide attenuation of X-rays in direct proportion to the concentration of iohexol. Since concentration changes over time, iohexol provides time-dependent image contrast which may assist in visualizing body structures.

12.2 Pharmacodynamics

Intrathecal Administration

The initial concentration and volume of the contrast medium, in conjunction with patient manipulation and the volume of cerebrospinal fluid (CSF) into which the contrast medium is placed, will determine the extent of the contrast that can be achieved. Following intrathecal injection in conventional radiography, OMNIPAQUE 180 mg iodine/mL, 240 mg iodine/mL, and 300 mg iodine/mL will continue to provide contrast for at least 30 minutes. Slow diffusion of iohexol takes place throughout the CSF with subsequent absorption into the bloodstream. At approximately 1 hour following injection, contrast will no longer be sufficient for conventional myelography.

After administration into the lumbar subarachnoid space, computerized tomography shows the presence of contrast medium in the thoracic region in about 1 hour, in the cervical region in about 2 hours, and in the basal cisterns in 3 to 4 hours.

Intravenous or Intra-arterial Administration

Following intravenous or intra-arterial administration of OMNIPAQUE, the degree of contrast enhancement is directly related to the iodine concentration of an administered dose; peak iodine blood concentrations occur immediately (15 seconds to 120 seconds) following rapid intravenous injection. The time to maximum contrast enhancement can vary, depending on the organ, from the time that peak blood iodine concentrations are reached to one hour after intravenous bolus administration. When a delay between peak blood iodine concentrations and peak contrast is present, it suggests that radiographic contrast enhancement is at least in part dependent on the accumulation of iodine containing agent within the lesion and outside the blood pool.

Oral Administration

Orally administered OMNIPAQUE produces visualization of the gastrointestinal tract. Less than 1% of orally administered iohexol is recovered in the urine, suggesting minimal amounts are absorbed from the normal gastrointestinal tract. This amount may increase in the presence of bowel perforation or bowel obstruction.

Intraarticular Administration

Visualization of the joint spaces can be accomplished by direct injection of contrast medium. For intraarticular cavities, the injected iohexol is absorbed into the surrounding tissue and subsequently absorbed into systemic circulation.

Body Cavity Administration

For most body cavities, the injected iohexol is absorbed into the surrounding tissue and subsequently absorbed into systemic circulation. Examinations of the uterus (hysterosalpingography) and bladder (voiding cystourethrography) involve the almost immediate drainage of contrast medium from the cavity upon conclusion of the radiographic procedure.

12.3 Pharmacokinetics

Following the intravenous administration of iohexol (between 500 mg iodine/kg to 1,500 mg iodine/kg) to 16 adult subjects, apparent first-order terminal elimination half-life was 12.6 hours and total body clearance was 131 (98 to 165) mL/min. Clearance was not dose dependent.

Absorption

As evidenced by the amount recovered in urine, <1% of orally administered iohexol is absorbed from the normal gastrointestinal tract. This amount may increase in the presence of bowel perforation or bowel obstruction.

Distribution

In 16 adult subjects (receiving between 500 mg iodine/kg to 1,500 mg iodine/kg intravenous iohexol) the plasma volume of distribution was165 (108 to 219) mL/kg.

In five adult patients receiving 16 mL to 18 mL of OMNIPAQUE (180 mg iodine/mL) by lumbar intrathecal injection the plasma volume of distribution was 559 (350 to 849) mL/kg.

Elimination

Metabolism

No significant metabolism, deiodination or biotransformation occurs.

Excretion

Following intravenous, intra-arterial or intrathecal administration, iohexol is excreted unchanged by glomerular filtration. Approximately 90% of the intravenously injected iohexol dose is excreted within the first 24 hours. Following intravenous or intraarterial administration, peak urine concentration occurs in the first hour after injection.

13 NONCLINICAL TOXICOLOGY

13.1 Carcinogenesis, Mutagenesis, Impairment of Fertility

Long-term animal studies have not been performed with iohexol to evaluate carcinogenic potential. Iohexol was not genotoxic in a series of studies, including the Ames test, the mouse lymphoma TK locus forward mutation assay, and a mouse micronucleus assay. Iohexol did not impair the fertility of male or female rats when repeatedly administered at intravenous dosages up to 4 g iodine/kg.

14 CLINICAL STUDIES

The safety and effectiveness of OMNIPAQUE for CT of the head were evaluated in three clinical studies. Each study also used an ionic high-osmolar iodinated contrast agent as a comparator. A total of 280 patients were randomized to administration of either OMNIPAQUE (n=142) or the comparator (n=138). OMNIPAQUE patients had a mean age of 52 years (range 16 to 85), 41% were women, and were administered a mean of 692 mg iodine/kg (range 337 to 1,250 mg iodine/kg) by intravenous injection with OMNIPAQUE 240 mg iodine/mL (1 study) or 300 mg iodine/mL (2 studies).

Efficacy was determined from investigator ratings of quality of contrast enhancement (none, poor, good, or excellent; only scans rated as good or excellent were considered diagnostic).

The percentage of OMNIPAQUE-enhanced scans rated as good or excellent was 100% in the two studies using OMNIPAQUE 300 mg iodine/mL, and 79% in the third study using OMNIPAQUE 240 mg iodine/mL.

16 HOW SUPPLIED/STORAGE AND HANDLING

How Supplied

OMNIPAQUE (iohexol) injection and OMNIPAQUE (iohexol) oral solution are colorless to pale yellow solutions available in the following presentations:

Dosage Form | Concentration (mg iodine/mL) | Package Size | Package Type & Material | Sale Unit | NDC
Injection | 140 | 50 mL | Single-Dose Polymer Bottles | Boxes of 10 | 0407-1401-52
Injection | 180 | 10 mL | Single-Dose Glass Vials | Boxes of 10 | 0407-1411-10
Injection | 240 | 10 mL | Single-Dose Glass Vials | Boxes of 10 | 0407-1412-10
Injection | 240 | 20 mL | Single-Dose Glass Vials | Boxes of 10 | 0407-1412-20
Injection | 240 | 50 mL | Single-Dose Polymer Bottles | Boxes of 10 | 0407-1412-30
Injection | 240 | 100 mL | Single-Dose Polymer Bottles | Boxes of 10 | 0407-1412-33
Injection | 300 | 10 mL | Single-Dose Glass Vials | Boxes of 10 | 0407-1413-10
Injection | 300 | 30 mL | Single-Dose Polymer Bottles | Boxes of 10 | 0407-1413-59
Injection | 300 | 50 mL | Single-Dose Polymer Bottles | Boxes of 10 | 0407-1413-61
Injection | 300 | 100 mL | Single-Dose Polymer Bottles | Boxes of 10 | 0407-1413-63
Injection | 300 | 125 mL | Single-Dose Glass Bottles | Boxes of 10 | 0407-1413-53
Injection | 300 | 150 mL | Single-Dose Polymer Bottles | Boxes of 10 | 0407-1413-65
Injection | 300 | 500 mL [OMNIPAQUE injection 300 mg iodine/mL and OMNIPAQUE injection 350 mg iodine/mL in bottles of 500 mL can be used as either an Imaging Bulk Package or a Pharmacy Bulk Package [see Dosage and Administration (2.10, 2.11)].] | Imaging or Pharmacy Bulk Package Polymer Bottles | Boxes of 10 | 0407-1413-72
Injection | 350 | 50 mL | Single-Dose Polymer Bottles | Boxes of 10 | 0407-1414-89
Injection | 350 | 75 mL | Single-Dose Polymer Bottles | Boxes of 10 | 0407-1414-90
Injection | 350 | 100 mL | Single-Dose Polymer Bottles | Boxes of 10 | 0407-1414-91
Injection | 350 | 125 mL | Single-Dose Glass Bottles | Boxes of 10 | 0407-1414-76
Injection | 350 | 150 mL | Single-Dose Polymer Bottles | Boxes of 10 | 0407-1414-93
Injection | 350 | 200 mL | Single-Dose Polymer Bottles | Boxes of 10 | 0407-1414-94
Injection | 350 | 500 mL | Imaging or Pharmacy Bulk Package Polymer Bottles | Boxes of 10 | 0407-1414-72
Oral Solution | 9 | 500 mL | Single-Dose Polymer Bottles | Boxes of 10 | 0407-1415-09
Oral Solution | 12 | 500 mL | Single-Dose Polymer Bottles | Boxes of 10 | 0407-1416-12

The container closure system components (bottle, vial, stopper, and cap) of OMNIPAQUE injection and OMNIPAQUE oral solution are not made with natural rubber latex.

Storage and Handling

- OMNIPAQUE Injection: Store at 20°C to 25°C (68°F to 77°F); excursions permitted to 15°C to 30°C (59°F to 86°F) [see USP Controlled Room Temperature]. May be stored in a contrast media warmer for up to one month, not to exceed 37°C (98.6°F).
- OMNIPAQUE Oral Solution: Store between 0°C and 30°C (32°F to 86°F).

Protect from light. Do not freeze. Discard any product that is inadvertently frozen, as freezing may compromise the closure integrity of the immediate container.

17 PATIENT COUNSELING INFORMATION

Hypersensitivity Reactions

Advise the patient concerning the risk of hypersensitivity reactions that can occur both during and after OMNIPAQUE administration. Advise the patient to report any signs or symptoms of hypersensitivity reactions during the procedure and to seek immediate medical attention for any signs or symptoms experienced after discharge [see Warnings and Precautions (5.3)].

Advise patients to inform their physician if they develop a rash after receiving OMNIPAQUE [see Warnings and Precautions (5.12)].

Acute Kidney Injury

Advise the patient concerning appropriate hydration to decrease the risk of contrast-induced acute kidney injury [see Warnings and Precautions (5.4)].

Extravasation

If extravasation occurs during injection, advise patients to seek medical care for progression of symptoms [see Warnings and Precautions (5.7)].

Lactation

Advise a lactating woman that interruption of breastfeeding is not necessary. However, to avoid any exposure, a lactating woman may consider pumping and discarding breast milk for 10 hours after OMNIPAQUE administration [see Use in Specific Populations (8.2)].

Thyroid Dysfunction

Advise parents/caregivers about the risk of developing thyroid dysfunction after OMNIPAQUE administration. Advise parents/caregivers about when to seek medical care for their child to monitor for thyroid function [see Warnings and Precautions (5.9)].

Distributed by GE Healthcare Inc., Marlborough, MA 01752 U.S.A.

OMNIPAQUE is a trademark of GE HealthCare or one of its subsidiaries.
GE is a trademark of General Electric Company used under trademark license.

© 2024 GE HealthCare

PRINCIPAL DISPLAY PANEL - 140 mgI/mL Bottle Label

NDC 0407-1401-52
50 mL

OMNIPAQUE™
(iohexol) Injection

140 mgI/mL

NOT FOR INTRATHECAL USE

in +PLUSPAK™ (polymer bottle)

PRINCIPAL DISPLAY PANEL - 180 mgI/mL Vial Label

GE Healthcare
NDC 0407-1411-20
20 mL

OMNIPAQUE™
(iohexol) Injection

180 mgI/mL

Single-Dose Vial
Sterile Aqueous Solution

Each 1 mL contains 388.3 mg of
iohexol (180 mg organically
bound iodine), 1.21 mg tromethamine,
and 0.1 mg edetate calcium disodium.

PRINCIPAL DISPLAY PANEL - 240 mgI/mL Bottle Label

NDC 0407-1412-34
150 mL

OMNIPAQUE™
(iohexol) Injection

240 mgI/mL

in +PLUSPAK™ (polymer bottle)

Single-Dose Bottle.
Sterile Aqueous Solution
For Injection or Oral Use.

DO NOT USE IF TAMPER-EVIDENT
RING IS BROKEN OR MISSING

PRINCIPAL DISPLAY PANEL - 300 mg Iodine/mL Bottle Label

NDC 0407-1413-65
150 mL

OMNIPAQUE™
(iohexol) Injection

300 mg Iodine/mL

For Injection or Oral Use

Single-Dose Bottle
Sterile Aqueous Solution

DO NOT USE IF TAMPER-EVIDENT
RING IS BROKEN OR MISSING

PRINCIPAL DISPLAY PANEL - 350 mgI/mL Bottle Label

NDC 0407-1414-93
150 mL

OMNIPAQUE™
(iohexol) Injection

350 mg Iodine/mL

For Intravascular, Oral,
Intraarticular, and
Body Cavity Use Only

Single-Dose Bottle
Sterile Aqueous Solution

NOT FOR INTRATHECAL USE

DO NOT USE IF TAMPER-EVIDENT
RING IS BROKEN OR MISSING

PRINCIPAL DISPLAY PANEL - 9 mg iodine/mL Bottle Label

NDC 0407-1415-09
500 mL

OMNIPAQUE™
(iohexol)
Oral Solution

9 mg iodine/mL

FOR ORAL USE ONLY

Single-Dose Bottle - Discard Unused Portion
Sterile Aqueous Solution - No Dilution Required

DO NOT USE IF TAMPER-EVIDENT RING IS BROKEN OR MISSING

PRINCIPAL DISPLAY PANEL - 12 mg iodine/mL Bottle Label

NDC 0407-1416-12
500 mL

OMNIPAQUE™
(iohexol)
Oral Solution

12 mg iodine/mL

FOR ORAL USE ONLY

Single-Dose Bottle - Discard Unused Portion
Sterile Aqueous Solution - No Dilution Required

DO NOT USE IF TAMPER-EVIDENT RING IS BROKEN OR MISSING